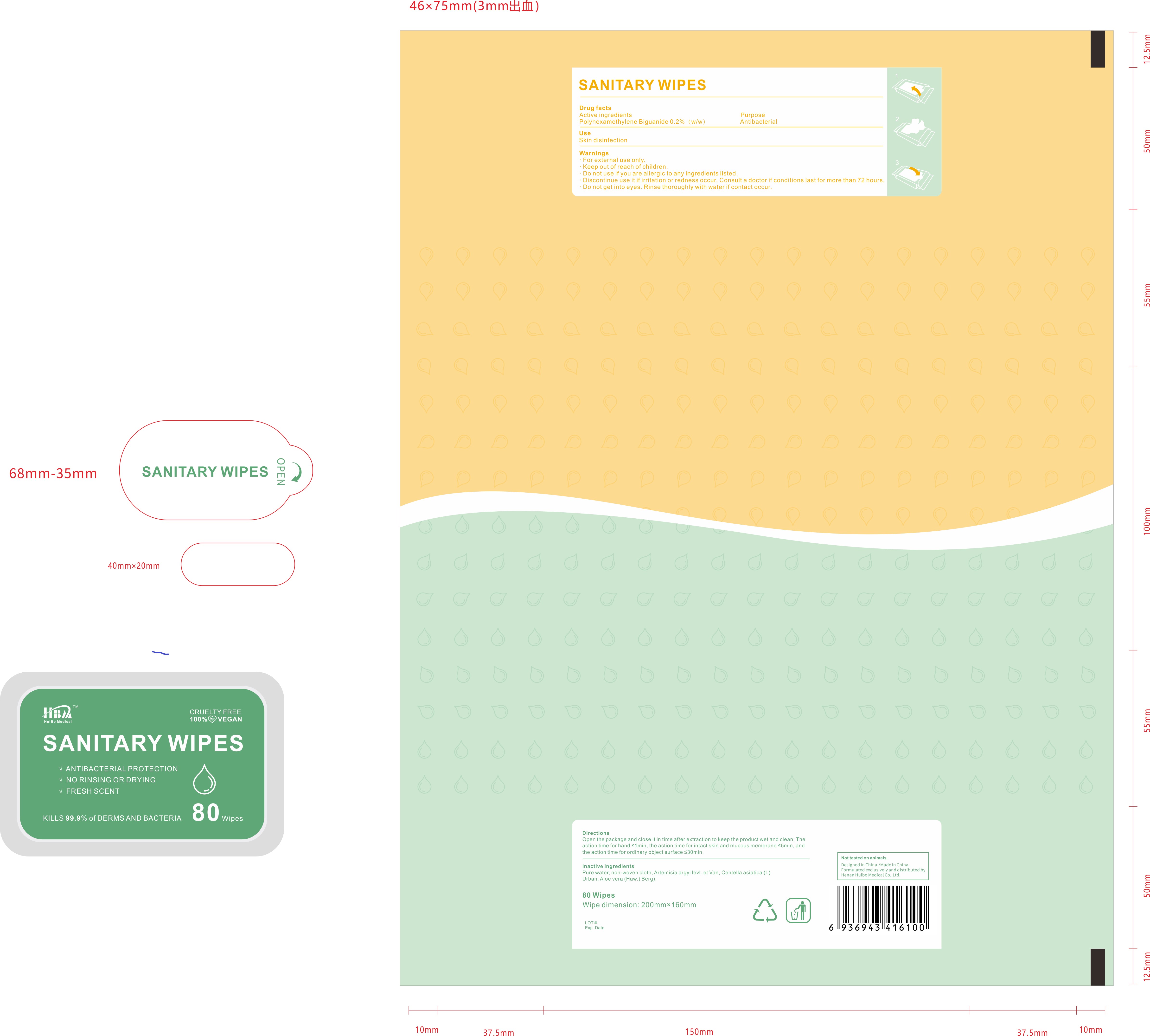 DRUG LABEL: HBA Sanitary Wipes
NDC: 79158-004 | Form: SOLUTION
Manufacturer: Henan Huibo Medical Co., Ltd.
Category: otc | Type: HUMAN OTC DRUG LABEL
Date: 20200722

ACTIVE INGREDIENTS: POLIHEXANIDE 5.44 mg/1 1
INACTIVE INGREDIENTS: WATER; ALOE VERA WHOLE; ARTEMISIA ARGYI WHOLE; CENTELLA ASIATICA

POLIHEXANIDE Wipes

Active Ingredient

polyhexamethylene biguanide 0.2% w/w

Purpose

Antibacterial

Use

■ Skin disinfection

WARNINGS

For external use only

Do not use if you are allergic to any ingredients listed

Discontinue use if irritation or redness occur. Consult a doctor if condition lasts for more than 72 hours

Do not get into eyes. Rinse thoroughly with water if contact occurs

keep out of reach of children

Directions

Open the package and close it in time after extraction to keep the product wet and clean. The action time for hands < 1 min, the action time for intact skin and mucous membrane < 5 min, and the action time for ordinary object surface < 30 min

Inactive ingredients

Water, Artemisia argyi levi. et Van, Centella asiatica (i.) Urban, Aloe vera (Haw.) Berg